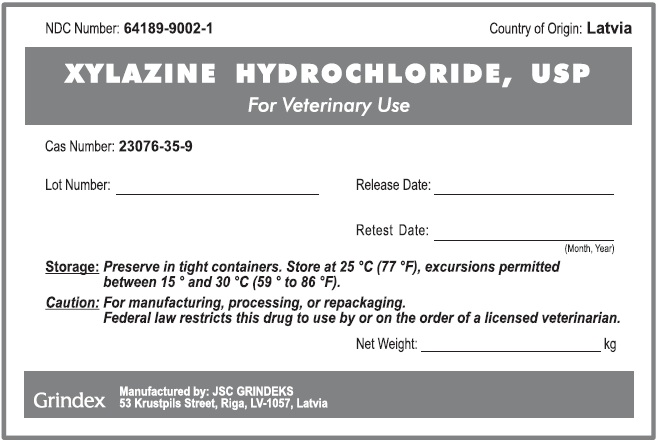 DRUG LABEL: Xylazine Hydrochloride
NDC: 64189-9002 | Form: POWDER
Manufacturer: GRINDEKS Joint Stock Company
Category: other | Type: BULK INGREDIENT - ANIMAL DRUG
Date: 20251216

ACTIVE INGREDIENTS: XYLAZINE HYDROCHLORIDE 1 kg/1 kg

Xylazine Hydrochloride

WARNINGS AND PRECAUTIONS

Caution: For manufacturing, processing, or repackaging.

Federal Law restricts this drug to use by or on the order of a licensed veterinarian.

STORAGE AND HANDLING

Storage: Preserve in tight containers. Store at 25°C (77°F), excursions permitted between 15° and 30°C (59° to 86°F).

PACKAGE LABEL

NDC Number: 64189-9002-1 Country of Origin: Latvia

XYLAZINE HYDROCHLORIDE, USP

For Veterinary Use

Cas Number: 23076-35-9

Lot Number:_______________ Release Date:____________

Retest Date:_____________

Storage: Preserve in tight containers. Store at 25°C (77°F), excursions permitted between 15° and 30°C (59° to 86°F).

Caution: For manufacturing, processing, or repackaging. Federal law restricts this drug to use by or on the order of a licensed veterinarian.

Net Weight:______________kg

Grindex

Manufactured by: JSC Grindeks

53 Krustpils Street, Riga, LV-1057, Latvia